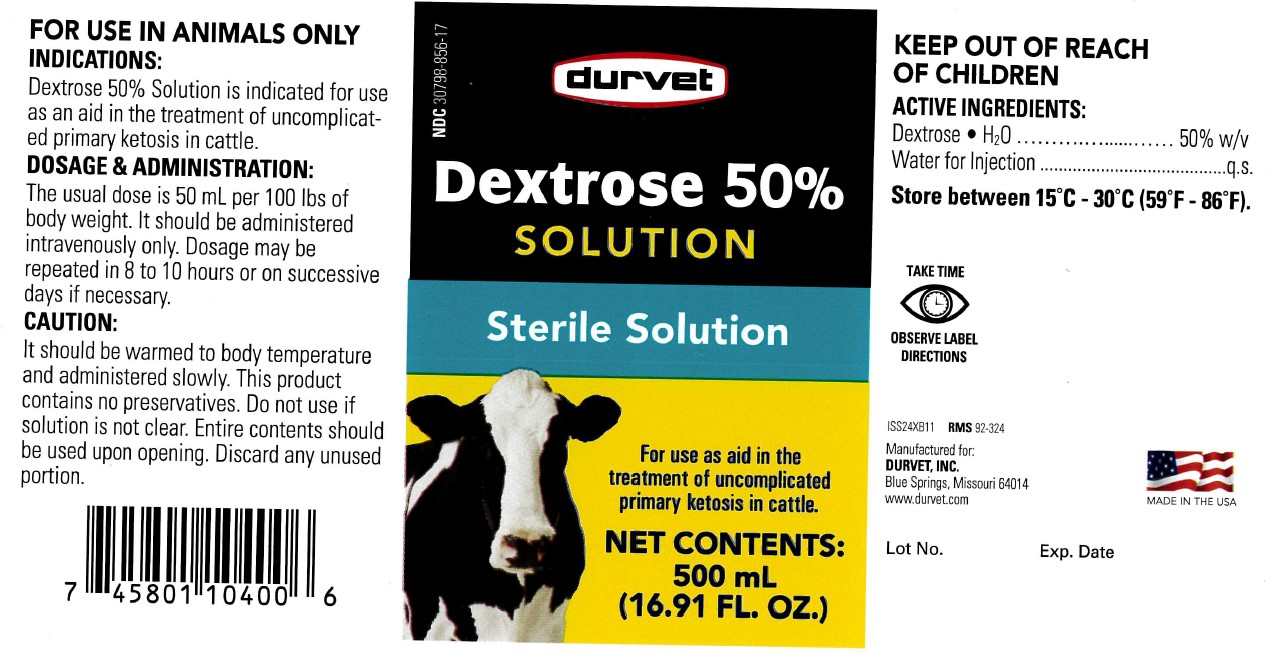 DRUG LABEL: Dextrose
NDC: 30798-856 | Form: INJECTION, SOLUTION
Manufacturer: Durvet
Category: animal | Type: OTC ANIMAL DRUG LABEL
Date: 20250728

ACTIVE INGREDIENTS: DEXTROSE MONOHYDRATE 50 g/100 mL

Dextrose 50%

Keep out of reach of children

ACTIVE INGREDIENTS:

Dextrose • H2 O .......................... 50% w/v

Water for Injection ........................... q.s.

DOSAGE AND ADMINISTRATION:

The usual dose is 50 mL per 100 lbs of body weight. It should be administered intravenously only. Dosage may be repeated in 8 to 10 hours or on successive days if necessary.

CAUTION:

It should be warmed to body temperature and administered slowly. This product contains no preservatives. Do not use if solution is not clear. Entire contents should be used upon opening. Discard any unused portion.

INDICATIONS:

Dextrose 50% Solution is indicated for use as an aid in the treatment of uncomplicated primary ketosis in cattle.

VETERINARY INDICATIONS

FOR USE IN ANIMALS ONLY

STORAGE AND HANDLING

Store between 15°C - 30°C (59°F - 86°F).

SAFE HANDLING WARNING

Take Time Observe Label Directions.

INFORMATION FOR OWNERS/CAREGIVERS

Made in the USA

STERILE SOLUTION

Net Contents:

500 mL (16.91 FL. OZ)

NDC 30798-856-17

ISS24XB11 RMS 92-324

Manufactured for:

Durvet, INC.

Blue Springs, Missouri 64014

www.durvet.com

Lot No. Exp. Date

INDICATIONS AND USAGE

For use as aid in the treatment of uncomplicated primary ketosis in cattle.